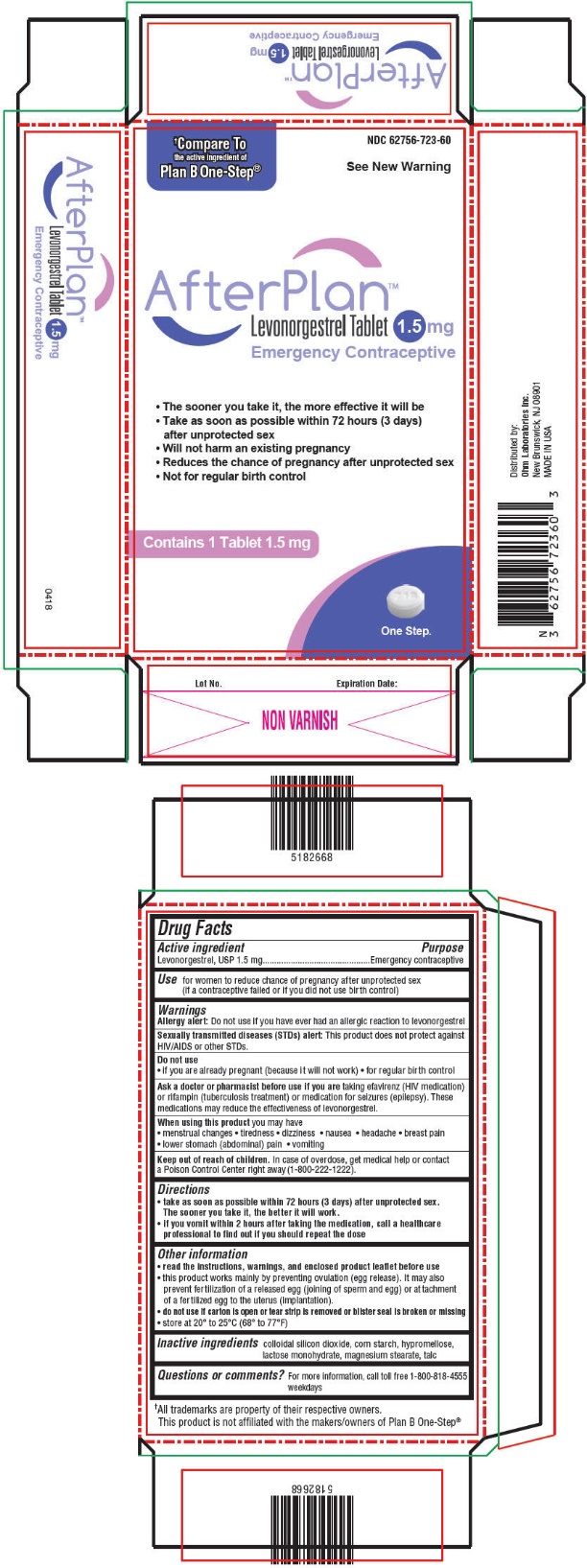 DRUG LABEL: AfterPlan
NDC: 62756-723 | Form: TABLET
Manufacturer: SUN PHARMACEUTICAL INDUSTRIES, INC.
Category: otc | Type: HUMAN OTC DRUG LABEL
Date: 20181026

ACTIVE INGREDIENTS: LEVONORGESTREL 1.5 mg/1 1
INACTIVE INGREDIENTS: SILICON DIOXIDE; STARCH, CORN; HYPROMELLOSE, UNSPECIFIED; LACTOSE MONOHYDRATE; MAGNESIUM STEARATE; TALC

AfterPlan™

Drug Facts

Active ingredient

Levonorgestrel, USP 1.5 mg

Purpose

Emergency contraceptive

Use

for women to reduce chance of pregnancy after unprotected sex (if a contraceptive failed or if you did not use birth control)

Warnings

Allergy alert

Do not use if you have ever had an allergic reaction to levonorgestrel

Sexually transmitted diseases (STDs) alert

This product does not protect against HIV/AIDS or other STDs.

Do not use

1. if you are already pregnant (because it will not work)
2. for regular birth control

Ask a doctor or pharmacist before use if you are taking efavirenz (HIV medication) or rifampin (tuberculosis treatment) or medication for seizures (epilepsy). These medications may reduce the effectiveness of levonorgestrel.

When using this product you may have

1. menstrual changes
2. tiredness
3. dizziness
4. nausea
5. headache
6. breast pain
7. lower stomach (abdominal) pain
8. vomiting

Keep out of reach of children. In case of overdose, get medical help or contact a Poison Control Center right away (1-800-222-1222).

Directions

1. take as soon as possible within 72 hours (3 days) after unprotected sex. The sooner you take it, the better it will work.
2. if you vomit within 2 hours after taking the medication, call a healthcare professional to find out if you should repeat the dose

Other information

1. read the instructions, warnings, and enclosed product leaflet before use
2. this product works mainly by preventing ovulation (egg release). It may also prevent fertilization of a released egg (joining of sperm and egg) or attachment of a fertilized egg to the uterus (implantation).
3. do not use if carton is open or tear strip is removed or blister seal is broken or missing
4. store at 20° to 25°C (68° to 77°F)

Inactive ingredients

colloidal silicon dioxide, corn starch, hypromellose, lactose monohydrate, magnesium stearate, talc

Questions or comments?

For more information, call toll free 1-800-818-4555 weekdays

Distributed by:
Ohm Laboratories Inc.
New Brunswick, NJ 08901

LEVONORGESTREL TABLET, 1.5 mg

Emergency Contraceptive

One Tablet. One Step.
What You Need to Know

What is levonorgestrel tablet?

Levonorgestrel tablet is emergency contraception that helps prevent pregnancy after birth control failure or unprotected sex. It is a backup method of preventing pregnancy and should not be used as regular birth control.

What levonorgestrel tablet is not.

Levonorgestrel tablet will not work if you are already pregnant and will not affect an existing pregnancy. Levonorgestrel tablet will not protect you from HIV infection (the virus that causes AIDS) and other sexually transmitted diseases (STDs).

When should I use levonorgestrel tablet?

The sooner you take emergency contraception, the better it works. You should use levonorgestrel tablet within 72 hours (3 days) after you have had unprotected sex.

Levonorgestrel tablet is a backup or emergency method of birth control you can use when:

1. your regular birth control was used incorrectly or failed
2. you did not use any birth control method

When not to use levonorgestrel tablet.

Levonorgestrel tablet should not be used:

1. as a regular birth control method, because it's not as effective as regular birth control.
2. if you are already pregnant, because it will not work.
3. if you are allergic to levonorgestrel or any other ingredients in levonorgestrel tablet.

When should I talk to a doctor or pharmacist?

Ask a doctor or pharmacist before use if you are taking efavirenz (HIV medication) or rifampin (tuberculosis treatment) or medication for seizures (epilepsy). These medications may reduce the effectiveness of levonorgestrel tablet and increase your chance of becoming pregnant. Your doctor may prescribe another form of emergency contraception that may not be affected by these medications.

How does levonorgestrel tablet work?

Levonorgestrel tablet is one tablet with levonorgestrel, a hormone that has been used in many birth control pills for several decades. Levonorgestrel tablet contains a higher dose of levonorgestrel than birth control pills, but works in a similar way to prevent pregnancy. It works mainly by stopping the release of an egg from the ovary. It is possible that levonorgestrel tablet may also work by preventing fertilization of an egg (the uniting of sperm with the egg) or by preventing attachment (implantation) to the uterus (womb).

How can I get the best results from levonorgestrel tablet?

You have 72 hours (3 days) to try to prevent pregnancy after birth control failure or unprotected sex. The sooner you take levonorgestrel tablet, the better it works.

How effective is levonorgestrel tablet?

If levonorgestrel tablet is taken as directed, it can significantly decrease the chance that you will get pregnant. About 7 out of every 8 women who would have gotten pregnant will not become pregnant.

How will I know levonorgestrel tablet worked?

You will know levonorgestrel tablet has been effective when you get your next period, which should come at the expected time, or within a week of the expected time. If your period is delayed beyond 1 week, it is possible you may be pregnant. You should get a pregnancy test and follow up with your healthcare professional.

Will I experience any side effects?

1. some women may have changes in their period, such as a period that is heavier or lighter or a period that is early or late. If your period is more than a week late, you may be pregnant.
2. if you have severe abdominal pain, you may have an ectopic pregnancy, and should get immediate medical attention.
3. when used as directed, levonorgestrel tablet is safe and effective. Side effects may include changes in your period, nausea, lower stomach (abdominal) pain, tiredness, headache, dizziness, and breast tenderness.
4. if you vomit within 2 hours of taking the medication, call a healthcare professional to find out if you should repeat the dose.

What if I still have questions about levonorgestrel tablet?

If you have questions or need more information, call our toll-free number, 1-800-818-4555.

Other Information

Keep out of reach of children:

In case of overdose, get medical help or contact a Poison Control Center right away at 1-800-222-1222.

Do not use if the blister seal is opened.

Store at room temperature 20° to 25° C (68° to 77° F).

Active ingredient: levonorgestrel 1.5 mg

Inactive ingredients: colloidal silicon dioxide, hypromellose, magnesium stearate, talc, corn starch, lactose monohydrate

If you are sexually active, you should see a healthcare provider for routine checkups. Your healthcare provider will talk to you about and, if necessary, test you for sexually transmitted diseases, teach you about effective methods of routine birth control, and answer any other questions you may have.

Manufactured by:
Sun Pharmaceutical Industries Limited
Halol-Baroda Highway,
Halol-389 350, Gujarat, India.

March 2018

5182666

PRINCIPAL DISPLAY PANEL - 1.5 mg Tablet Blister Pack Carton

†Compare To
the active ingredient of
Plan B One-Step®

NDC 62756-723-60

See New Warning

AfterPlan™
Levonorgestrel Tablet 1.5 mg
Emergency Contraceptive

1. The sooner you take it, the more effective it will be
2. Take as soon as possible within 72 hours (3 days)
  after unprotected sex
3. Will not harm an existing pregnancy
4. Reduces the chance of pregnancy after unprotected sex
5. Not for regular birth control

Contains 1 Tablet 1.5 mg

One Step.